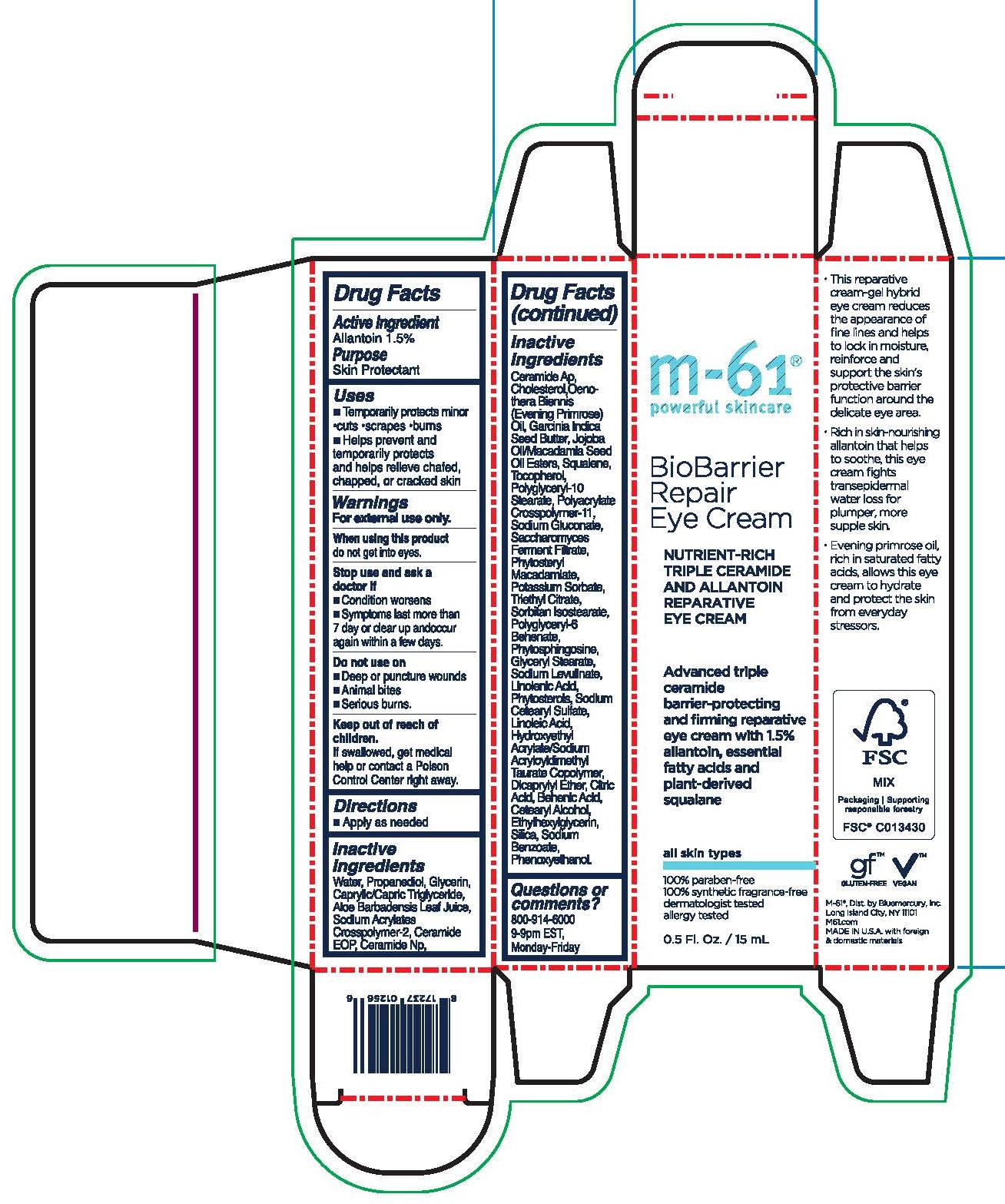 DRUG LABEL: BioBarrier Repair Eye Cream
NDC: 72203-020 | Form: CREAM
Manufacturer: Bluemercury Inc.
Category: otc | Type: HUMAN OTC DRUG LABEL
Date: 20240804

ACTIVE INGREDIENTS: ALLANTOIN 1.5 g/100 g
INACTIVE INGREDIENTS: JOJOBA OIL; DICAPRYLYL ETHER; ETHYLHEXYLGLYCERIN; SODIUM BENZOATE; GARCINIA INDICA SEED BUTTER; CHOLESTEROL; EVENING PRIMROSE OIL; POLYGLYCERYL-10 STEARATE; AMMONIUM ACRYLOYL DIMETHYLTAURATE/METHACRYLATE, DIMETHYLACRYLAMIDE AND METHACRYLIC ACID COPOLYMER, PPG-3 GLYCERYL TRIACRYLATE CROSSLINKED (100000 MW); SACCHAROMYCES CEREVISIAE; PHYTOSTERYL MACADAMIATE; POTASSIUM SORBATE; POLYGLYCERYL-6 BEHENATE; PHYTOSPHINGOSINE; GLYCERYL MONOSTEARATE; .BETA.-SITOSTEROL; HYDROXYETHYL ACRYLATE/SODIUM ACRYLOYLDIMETHYL TAURATE COPOLYMER (45000 MPA.S AT 1%); CITRIC ACID MONOHYDRATE; CETOSTEARYL ALCOHOL; SILICON DIOXIDE; CERAMIDE AP; MACADAMIA OIL; TOCOPHEROL; TRIETHYL CITRATE; SORBITAN ISOSTEARATE; SODIUM LEVULINATE; LINOLENIC ACID; SODIUM CETOSTEARYL SULFATE; LINOLEIC ACID; BEHENIC ACID; PHENOXYETHANOL; SQUALENE; SODIUM GLUCONATE

m-61 BioBarrier Repair Eye Cream

m-61

powerful skincare

BioBarrier Repair Eye Cream

NUTRIENT-RICH TRIPLE CERAMIDE AND ALLANTOIN REPARATIVE EYE CREAM

Advanced triple ceramide barrier-protecting and firming reparative eye cream with 1.5% allantoin, essential fatty acids and plant-derived squalane

all skin types

100% paraben-free

100% synthetic fragrance-free

dermatologist tested

allergy tested

0.5 Fl. Oz. / 15 mL

Active Ingredient

Allantoin 1.5%

Purpose

Skin Protectant

Uses

- Temporarily protects minor - cuts - scrapes - burns
- Helps prevent and temporarily protects and helps relieve chafed, chapped, or cracked skin.

Warnings

For external use only.

When using this product do not get into eyes.

Stop use and ask a doctor if

- Condition worsens
- Symptoms last more than 7 day or clear up and occur again within a few days

Do not use on

- Deep or puncture wounds
- Animal bites
- Serious burns

Keep out of reach of children.

If swallowed, get medical help or contact a Poison Control Center right away.

Directions

- Apply as needed

Inactive Ingredients

water, propanediol, glycerin, caprylic/capric triglyceride, aloe barbadensis leaf juice, sodium acrylates crosspolymer-2, ceramide eop, ceramide np, ceramide ap, cholesterol,oenothera biennis (evening primrose) oil, garcinia indica seed butter, jojoba oil/macadamia seed oil esters, squalene, tocopherol, polyglyceryl-10 stearate, polyacrylate crosspolymer-11, sodium gluconate, saccharomyces ferment filtrate, phytosteryl macadamiate, potassium sorbate, triethyl citrate, sorbitan isostearate, polyglyceryl-6 behenate, phytosphingosine, glyceryl stearate, sodium levulinate, linolenic acid, phytosterols, sodium cetearyl sulfate, linoleic acid, hydroxyethyl acrylate/sodium acryloyldimethyl taurate copolymer, dicaprylyl ether, citric acid, behenic acid, cetearyl alcohol, ethylhexylglycerin, silica, sodium benzoate, phenoxyethanol.

Questions or comments?

800-914-6000 9-9pm EST, Monday-Friday